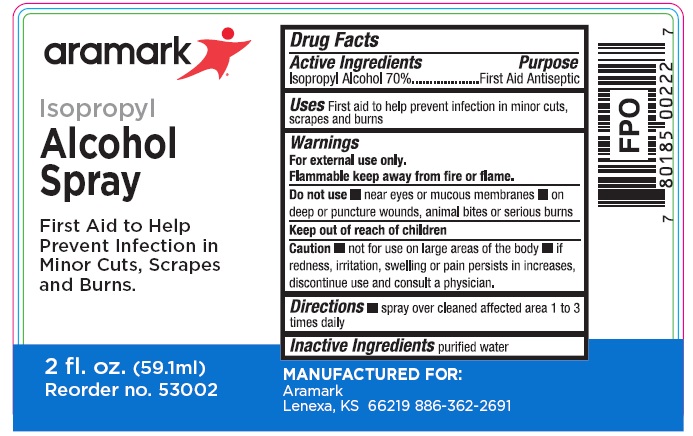 DRUG LABEL: Aramark Isopropyl
NDC: 81238-5500 | Form: SPRAY
Manufacturer: Western First Aid Safety DBA Aramark
Category: otc | Type: HUMAN OTC DRUG LABEL
Date: 20210526

ACTIVE INGREDIENTS: ISOPROPYL ALCOHOL 70 mL/100 mL
INACTIVE INGREDIENTS: WATER

aramark Isopropyl Alcohol Spray

Drug Facts

Active Ingredients

Isopropyl Alcohol 70%

Purpose

First Aid Antiseptic

Uses

First aid to help prevent infection in minor cuts,

scrapes and burns

Warnings

For external use only.

Flammable keep away from fire or flame.

Do not use

- near eyes or mucous membranes • on deep or

puncture wounds, animal bites, or serious burns

Keep out of reach of children

Caution • not for use on large areas of the body • if

redness, irritation, swelling or pain persists in increases,

discontinue use and consult a physician.

Directions

• spray over cleaned affected area 1 to 3 times daily

Inactive ingredients

purified water

Package Labeling

aramark

Isopropyl

Alcohol Spray

For Aid to Help
Prevent Infection in
Minor Cuts, Scrapes
and Burns

2 fl. oz. (59.1ml)
Reorder no. 53002

MANUFACTURED FOR:
Aramark
Lenexa, KS 66219 886-362-2691

res